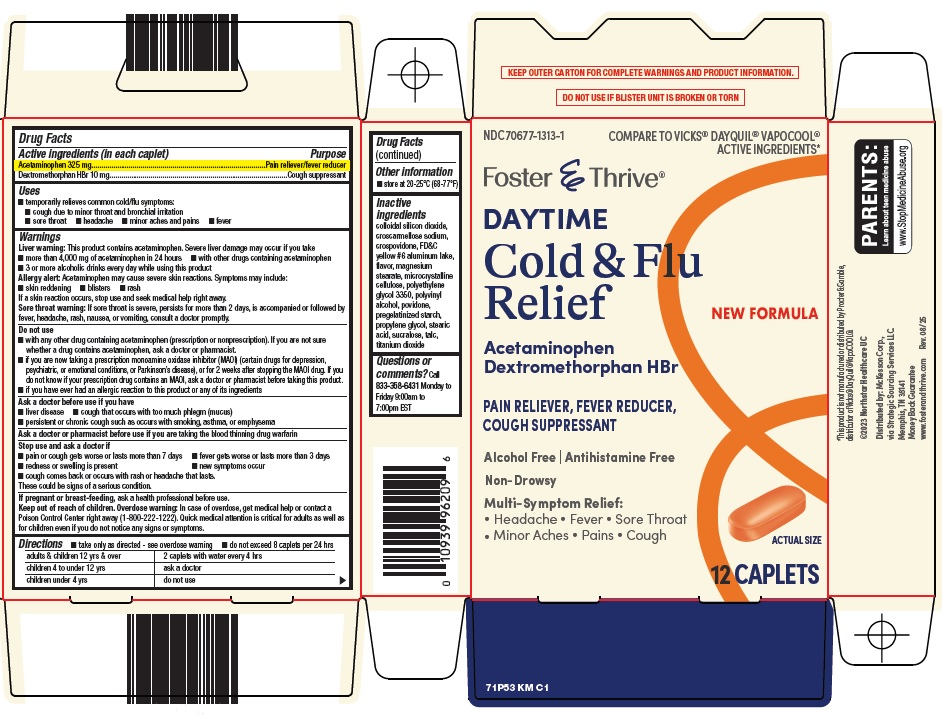 DRUG LABEL: Foster and Thrive Daytime Cold and Flu Relief
NDC: 70677-1313 | Form: TABLET, FILM COATED
Manufacturer: Strategic Sourcing Services LLC
Category: otc | Type: HUMAN OTC DRUG LABEL
Date: 20260118

ACTIVE INGREDIENTS: ACETAMINOPHEN 325 mg/1 1; DEXTROMETHORPHAN HYDROBROMIDE 10 mg/1 1
INACTIVE INGREDIENTS: SILICON DIOXIDE; CROSCARMELLOSE SODIUM; CROSPOVIDONE, UNSPECIFIED; FD&C YELLOW NO. 6 ALUMINUM LAKE; MAGNESIUM STEARATE; MICROCRYSTALLINE CELLULOSE; POLYETHYLENE GLYCOL 3350; POLYVINYL ALCOHOL, UNSPECIFIED; POVIDONE, UNSPECIFIED; PROPYLENE GLYCOL; STEARIC ACID; SUCRALOSE; TALC; TITANIUM DIOXIDE

McKesson DAYTIME Cold & Flu Relief Drug Facts

Active ingredients (in each caplet)

Acetaminophen 325 mg

Dextromethorphan HBr 10 mg

Purpose

Pain reliever/fever reducer

Cough suppressant

Uses

- temporarily relieves common cold/flu symptoms:
- cough due to minor throat and bronchial irritation
- sore throat
- headache
- minor aches and pains
- fever

Warnings

Liver warning: This product contains acetaminophen. Severe liver damage may occur if you take

- more than 4,000 mg of acetaminophen in 24 hours
- with other drugs containing acetaminophen
- 3 or more alcoholic drinks every day while using this product

Allergy alert: Acetaminophen may cause severe skin reactions. Symptoms may include:

- skin reddening
- blisters
- rash

If a skin reaction occurs, stop use and seek medical help right away.

Sore throat warning: If sore throat is severe, persists for more than 2 days, is accompanied or followed by fever, headache, rash, nausea, or vomiting, consult a doctor promptly.

Do not use

- with any other drug containing acetaminophen (prescription or nonprescription). If you are not sure whether a drug contains acetaminophen, ask a doctor or pharmacist.
- if you are now taking a prescription monoamine oxidase inhibitor (MAOI) (certain drugs for depression, psychiatric, or emotional conditions, or Parkinson’s disease), or for 2 weeks after stopping the MAOI drug. If you do not know if your prescription drug contains an MAOI, ask a doctor or pharmacist before taking this product.
- if you have ever had an allergic reaction to this product or any of its ingredients

Ask a doctor before use if you have

- liver disease
- cough that occurs with too much phlegm (mucus)
- persistent or chronic cough such as occurs with smoking, asthma, or emphysema

Ask a doctor or pharmacist before use if you are

taking the blood thinning drug warfarin

Stop use and ask a doctor if

- pain or cough gets worse or lasts more than 7 days
- fever gets worse or lasts more than 3 days
- redness or swelling is present
- new symptoms occur
- cough comes back or occurs with rash or headache that lasts.

These could be signs of a serious condition.

If pregnant or breast-feeding,

ask a health professional before use.

Keep out of reach of children.

Overdose warning: In case of overdose, get medical help or contact a Poison Control Center right away (1-800-222-1222). Quick medical attention is critical for adults as well as for children even if you do not notice any signs or symptoms.

Directions

- take only as directed - see overdose warning
- do not exceed 8 caplets per 24 hrs

adults & children 12 yrs & over | 2 caplets with water every 4 hrs
children 4 to under 12 yrs | ask a doctor
children under 4 yrs | do not use

Other information

- store at 20-25°C (68-77°F)

Inactive ingredients

colloidal silicon dioxide, croscarmellose sodium, crospovidone, FD&C yellow #6 aluminum lake, flavor, magnesium stearate, microcrystalline cellulose, polyethylene glycol 3350, polyvinyl alcohol, povidone, pregelatinized starch, propylene glycol, stearic acid, sucralose, talc, titanium dioxide

Questions or comments?

Call 833-358-6431 Monday to Friday 9:00am to 7:00pm EST

Package/Label Principal Display Panel

COMPARE TO VICKS® DAYQUIL® VAPOCOOL® ACTIVE INGREDIENTS

Foster & Thrive®

DAYTIME

Cold & Flu Relief

NEW FORMULA

Acetaminophen

Dextromethorphan HBr

PAIN RELIEVER, FEVER REDUCER, COUGH SUPPRESSANT

Alcohol Free | Antihistamine Free

Non-Drowsy

Multi-Symptom Relief:

• Headache • Fever • Sore Throat • Minor Aches • Pains • Cough

ACTUAL SIZE

12 CAPLETS